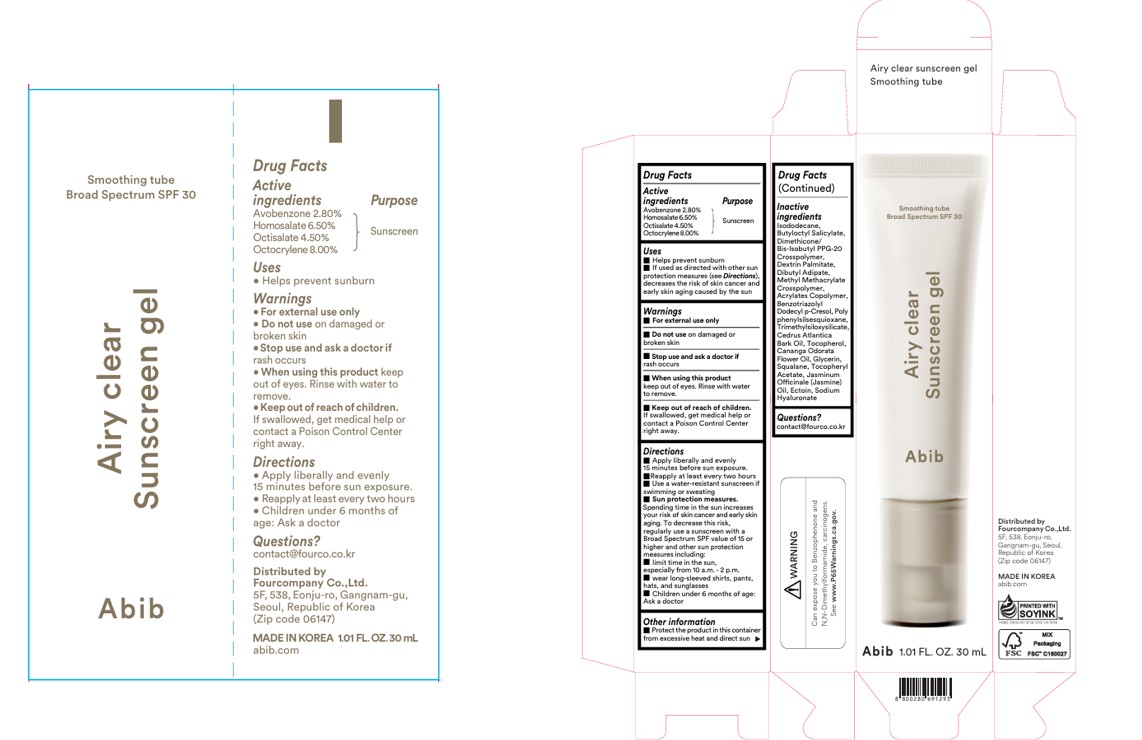 DRUG LABEL: Abib Airy clear sunscreen gel  Smoothing tube
NDC: 73676-100 | Form: GEL
Manufacturer: Fourcompany Co., Ltd.
Category: otc | Type: HUMAN OTC DRUG LABEL
Date: 20251210

ACTIVE INGREDIENTS: HOMOSALATE 65 mg/1 mL; AVOBENZONE 28 mg/1 mL; OCTOCRYLENE 80 mg/1 mL; OCTISALATE 45 mg/1 mL
INACTIVE INGREDIENTS: METHYL METHACRYLATE/GLYCOL DIMETHACRYLATE CROSSPOLYMER; GLYCERIN; ISODODECANE; DIMETHICONE/BIS-ISOBUTYL PPG-20 CROSSPOLYMER; DEXTRIN PALMITATE (CORN; 20000 MW); DIBUTYL ADIPATE; CANANGA ODORATA FLOWER OIL; POLYPHENYLSILSESQUIOXANE (RI 1.55); ECTOINE; .ALPHA.-TOCOPHEROL ACETATE; SQUALANE; BUTYL ACRYLATE/METHYL METHACRYLATE/METHACRYLIC ACID COPOLYMER (18000 MW); JASMINUM OFFICINALE FLOWER; BUTYLOCTYL SALICYLATE; SODIUM HYALURONATE; TRIMETHYLSILOXYSILICATE (M/Q 0.6-0.8); CEDRUS ATLANTICA BARK OIL; TOCOPHEROL; BENZOTRIAZOLYL DODECYL P-CRESOL

Active Ingredient

Homosalate 6.50%,
Octocrylene 8.00%,
Octisalate 4.50%,
Avobenzone 2.80%

Uses

1.Helps prevent sunburn

2.If used as directed with other sun protection measures (see Directions), decreases the risk of skin cancer and early skin aging caused by the sun

Do not use

Do not use on damaged or broken skin

Stop use

Stop use and ask a doctor if rash occurs

When using

When using this product keep out of eyes. Rinse with water to remove.

Keep out of reach of children

Keep out of reach of children. If swallowed, get medical help or contact a Poison Control Center
right away.

Directions

1.Apply liberally and evenly 15 minutes before sun exposure. Reapply at least every two hours

2.Use a water-resistant sunscreen if swimming or sweating

3.Sun protection measures.

Spending time in the sun increases your risk of skin cancer and early skin aging. To decrease this risk, regularly use a sunscreen with a Broad Spectrum SPF value of 15 or higher and other sun protection measures including:

■ limit time in the sun, especially from 10 a.m. - 2 p.m.
■ wear long-sleeved shirts, pants, hats, and sunglasses

4.Children under 6 months of age: Ask a doctor

Inactive Ingredient

Isododecane, Butyloctyl Salicylate, Dimethicone/Bis-Isobutyl PPG-20 Crosspolymer, Dextrin Palmitate, Dibutyl Adipate, Methyl Methacrylate Crosspolymer, Acrylates Copolymer, Benzotriazolyl Dodecyl p-Cresol, Polyphenylsilsesquioxane, Trimethylsiloxysilicate, Cedrus Atlantica Bark Oil, Tocopherol, Cananga Odorata Flower Oil, Glycerin, Squalane, Tocopheryl Acetate, Jasminum
Officinale (Jasmine) Oil, Ectoin, Sodium Hyaluronate

Warnings

- For external use only
- Do not use on damaged or broken skin
- Stop use and ask a doctor if rash occurs
- When using this product keep out of eyes. Rinse with water to remove.

Uses

- Helps prevent sunburn
- If used as directed with other sun protection measures (see Directions), decreases the risk of skin cancer and early skin aging caused by the sun

PACKAGE LABEL

Abib
Airy clear sunscreen gel
smoothing tube
Broad Spectrum SPF 30
1.01 FL. OZ. 30 mL